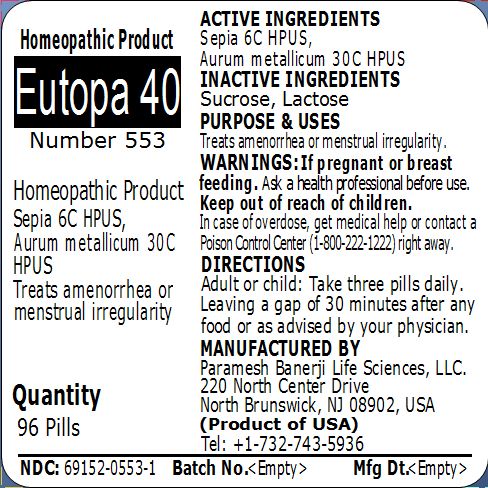 DRUG LABEL: Eutopa 40 (Number 553
NDC: 69152-0553 | Form: PELLET
Manufacturer: Paramesh Banerji Life Sciences LLC
Category: homeopathic | Type: HUMAN OTC DRUG LABEL
Date: 20150304

ACTIVE INGREDIENTS: SEPIA OFFICINALIS JUICE 6 [hp_C]/1 1; GOLD 30 [hp_C]/1 1
INACTIVE INGREDIENTS: SUCROSE; LACTOSE

Active Ingredients

Sepia 6C HPUS, Aurum metallicum 30C HPUS

Inactive Ingredients

Sucrose, Lactose

Purpose

Treats amenorrhea or menstrual irregularity

Uses

Treats amenorrhea or menstrual irregularity

Warnings

If pregnant or breast feeding ask a health professional before use.

Keep out of reach of children. In case of overdose, get medical help or contact a Poison Control Center (1-800-222-1222) right away.

Direction

Adult or child: Take three pills daily. Leaving a gap of 30 minutes after any food or as advised by your physician.

Manufactured by

Paramesh Banerji Life Sciences, LLC

220 North Center Drive

North Brunswick, NJ 08902, USA

Product of USA

Tel: +1-732-743-5936

Principal Display Panel

Homeopathic Product

Eutopa 40

Number 553

Homeopathic Product

Sepia 6C HPUS, Aurum metallicum 30C HPUS

Treats amenorrhea or menstrual irregularity

Quantity

96 Pills